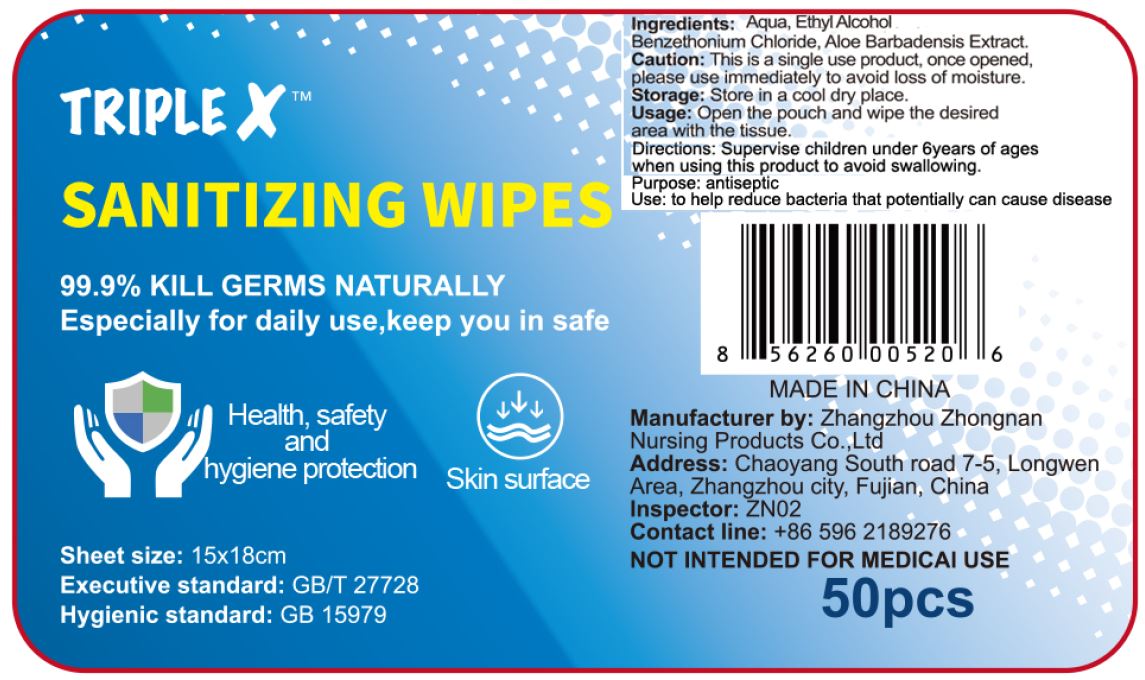 DRUG LABEL: Triple X Sanitizing Wipes
NDC: 79650-003 | Form: LIQUID
Manufacturer: Zhangzhou Zhongnan Nursing Products Co., Ltd.
Category: otc | Type: HUMAN OTC DRUG LABEL
Date: 20200811

ACTIVE INGREDIENTS: ALCOHOL 75 mL/100 mL
INACTIVE INGREDIENTS: BENZETHONIUM CHLORIDE; ALOE; WATER

Active Ingredients

Ethanol Alcohol 75%

Purpose

Antiseptic

Uses

To help reduce bacteria that potentially can cause disease

Directions

Open the pouch and wipe the desired area with the tissue.

Warnings

This is a single use product, once opened, please use immediately to avoid loss of moisture.

Keep Out of Reach of Children

Supervise children under 6 years of ages when using this product to avoid swallowing.

Storage

Store in a cool dry place.

Inactive Ingredients

Water, Benzethonium Chloride, Aloe Barbadensis Extract.

Package Label/Principal Display Panel

NDC 79650-003-07 (200 ml)